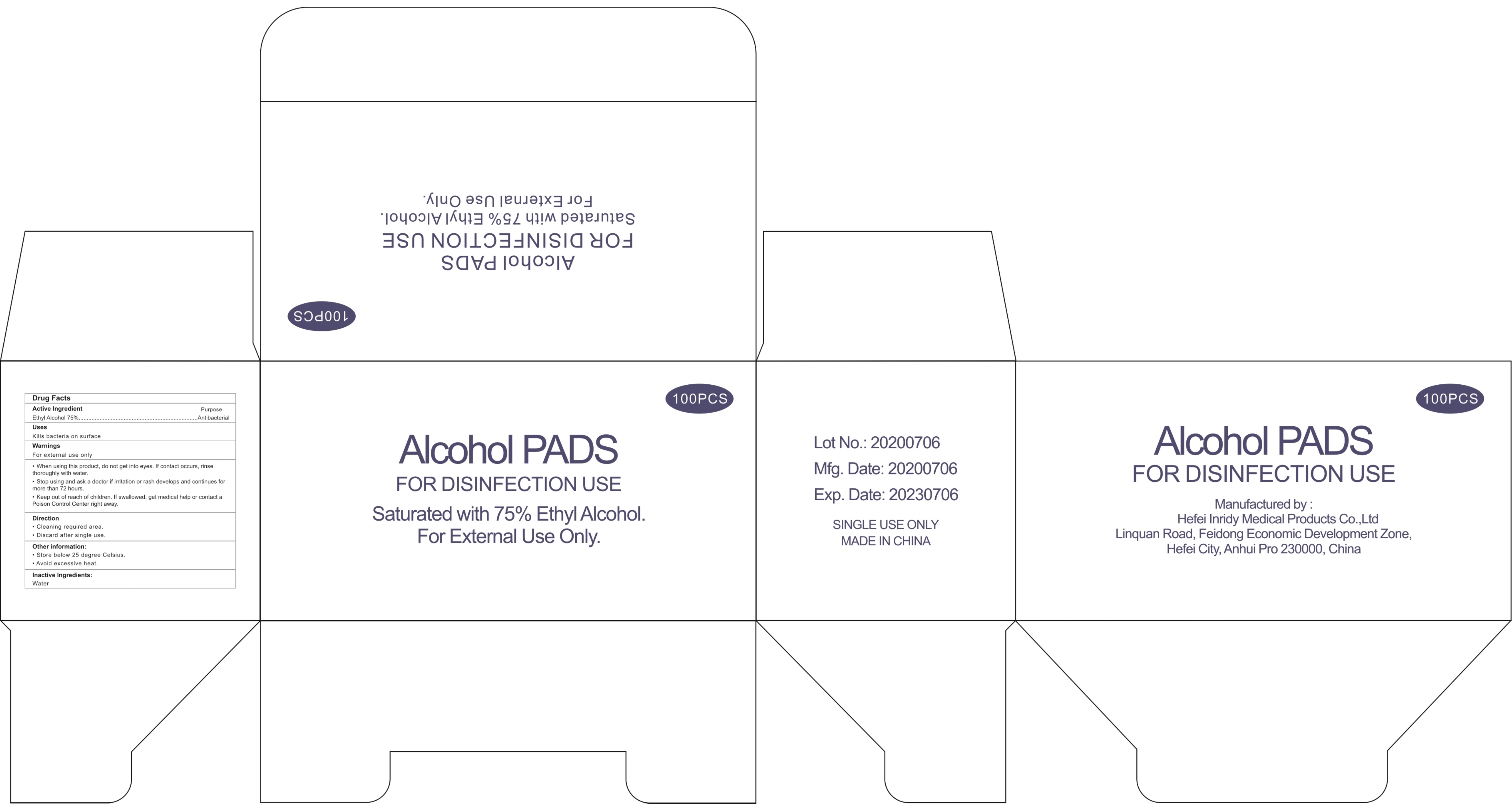 DRUG LABEL: Alcohol Pads
NDC: 79683-004 | Form: CLOTH
Manufacturer: Hefei Inridy Medical Products Co., Ltd
Category: otc | Type: HUMAN OTC DRUG LABEL
Date: 20200717

ACTIVE INGREDIENTS: ALCOHOL 75 1/100 1
INACTIVE INGREDIENTS: WATER

Alcohol Pads

Active Ingredient(s)

Ethyl Alcohol 75%

Purpose

Antibacterial

Use

Kills bacteria on surface

Warnings

For external use only

Do not use

/

When using this product, do not get into eyes. If contact occurs, rinse thoroughly with water

STOP USE

Stop using and ask a doctor if irritation or rash develops and continues for more than 72 hours

Keep out of reach of children. If swallowed, get medical help or contact a Poison Control Center right away

Directions

Cleaning required area.
Discard after single use.

Other information

Store below 25 degree Celsius.
Avoid excessive heat